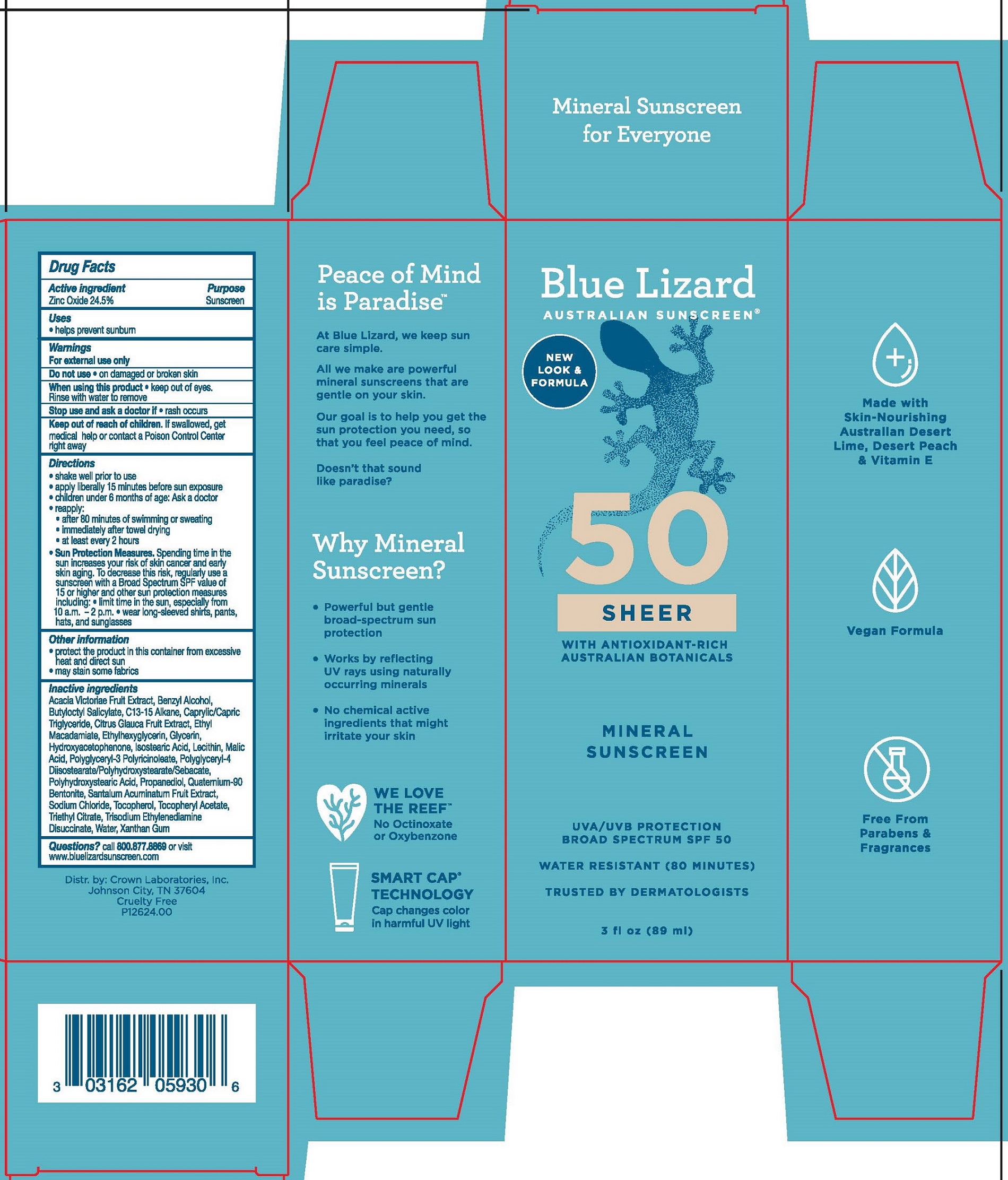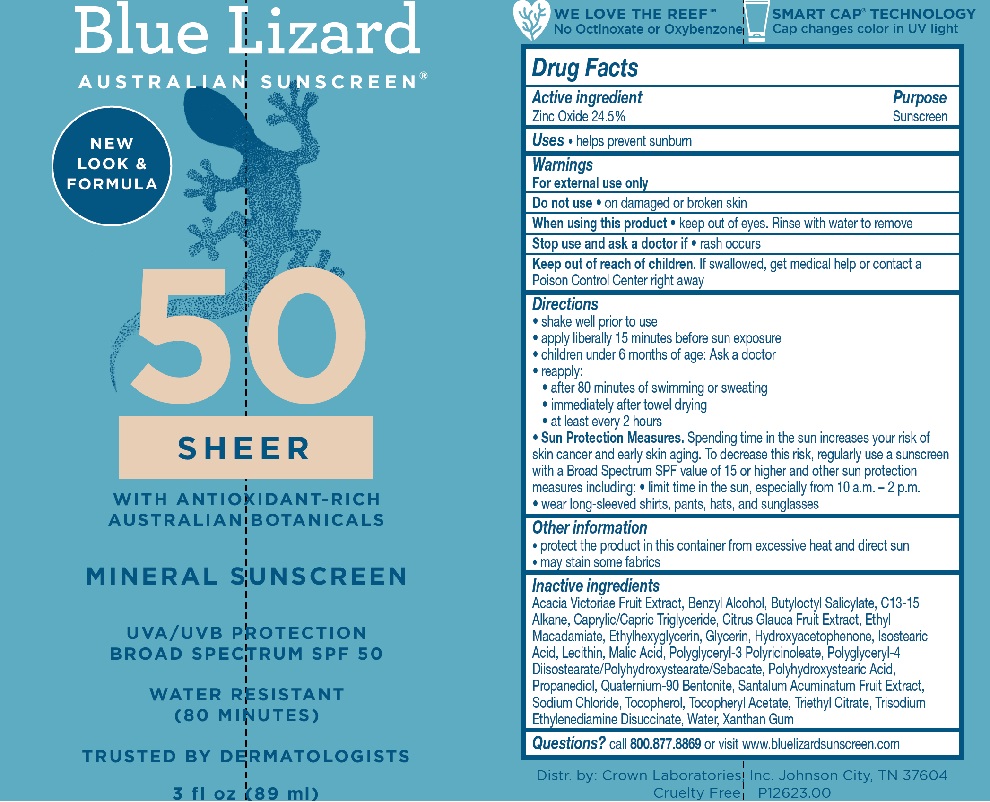 DRUG LABEL: Blue Lizard Sheer SPF 50 Sunscreen
NDC: 0316-2059 | Form: LOTION
Manufacturer: Crown Laboratories
Category: otc | Type: HUMAN OTC DRUG LABEL
Date: 20260112

ACTIVE INGREDIENTS: ZINC OXIDE 303.8 mg/1 mL
INACTIVE INGREDIENTS: CAPRYLIC/CAPRIC TRIGLYCERIDE; LECITHIN, SUNFLOWER; POLYGLYCERYL-3 PENTARICINOLEATE; POLYGLYCERYL-4 DIISOSTEARATE/POLYHYDROXYSTEARATE/SEBACATE; TOCOPHEROL; QUATERNIUM-90 BENTONITE; ISOSTEARIC ACID; C13-15 ALKANE; ETHYL MACADAMIATE; HYDROXYACETOPHENONE; PROPANEDIOL; SODIUM CHLORIDE; ACACIA VICTORIAE FRUIT; GLYCERIN; ETHYLHEXYLGLYCERIN; WATER; TRIETHYL CITRATE; XANTHAN GUM; .ALPHA.-TOCOPHEROL ACETATE; POLYHYDROXYSTEARIC ACID (2300 MW); CITRUS GLAUCA FRUIT; TRISODIUM ETHYLENEDIAMINE DISUCCINATE; BENZYL ALCOHOL; BUTYLOCTYL SALICYLATE; MALIC ACID; SANTALUM ACUMINATUM FRUIT

Blue Lizard Sheer Lotion SPF 50 Sunscreen

Active ingredients

Zinc Oxide 24.5%

Purpose

Sunscreen

Uses

- helps prevent sunburn

Warnings

For external use only

Do not use • on damaged or broken skin

When using this product • keep out of eyes. Rinse with water to remove

Stop use and ask doctor if • rash occurs

Keep out of reach of children. If swallowed, get medical help or contact a Poison Control Center right away

Directions

• shake well prior to use

• apply liberally 15 minutes before sun exposure

• children under 6 months of age: ask a doctor

• reapply:

• after 80 minutes of swimming or sweating

• immediately after towel drying

• at least every 2 hours

• Sun Protection Measures. Spending time in the sun increases your risk of skin cancer and early skin aging. To decrease this risk, regularly use a sunscreen with a Broad Spectrum SPF value of 15 or higher and other sun protection measures including: • limit time in the sun, especially from 10 a.m. - 2 p.m. • wear long-sleeved shirts, pants, hats, and sunglasses.

Other information

- protect the product in this container from excessive heat and direct sun
- may stain some fabrics

Inactive ingredients

Acacia Victoriae Fruit Extract, Benzyl Alcohol, Butyloctyl Salicylate, C13-15 Alkane, Caprylic/Capric Triglyceride, Citrus Glauca Fruit Extract, Ethyl Macadamiate, Ethylhexylglycerin, Glycerin, Hydroxyacetophenone, Isostearic Acid, Lecithin, Malic Acid, Polyglyceryl-3 Polyricinoleate, Polyglyceryl-4 Diisostearate/Polyhydroxystearate/Sebacate, Polyhydroxystearic Acid, Propanediol, Quaternium-90 Bentonite, Santalum Acuminatum Fruit Extract, Sodium Chloride, Tocopherol, Tocopheryl Acetate, Triethyl Citrate, Trisodium Ethylenediamine Disuccinate, Water, Xanthan Gum

Questions?

call 800.877.8869 or visit www.bluelizardsunscreen.com

Blue Lizard Sheer Lotion - 3oz Tube Label

Blue Lizard

AUSTRALIAN SUNSCREEN

50

SHEER

with antioxidant-rich Australian botanicals

MINERAL SUNSCREEN

UVA/UVB PROTECTION

BROAD SPECTRUM SPF 50

WATER RESISTANT (80 MINUTES)

TRUSTED BY DERMATOLOGISTS

3 fl oz (89 ml)

Blue Lizard Sheer Lotion - 3oz Carton

Blue Lizard

AUSTRALIAN SUNSCREEN

50

SHEER

with antioxidant-rich Australian botanicals

MINERAL SUNSCREEN

UVA/UVB PROTECTION

BROAD SPECTRUM SPF 50

WATER RESISTANT (80 MINUTES)

TRUSTED BY DERMATOLOGISTS

3 fl oz (89 ml)